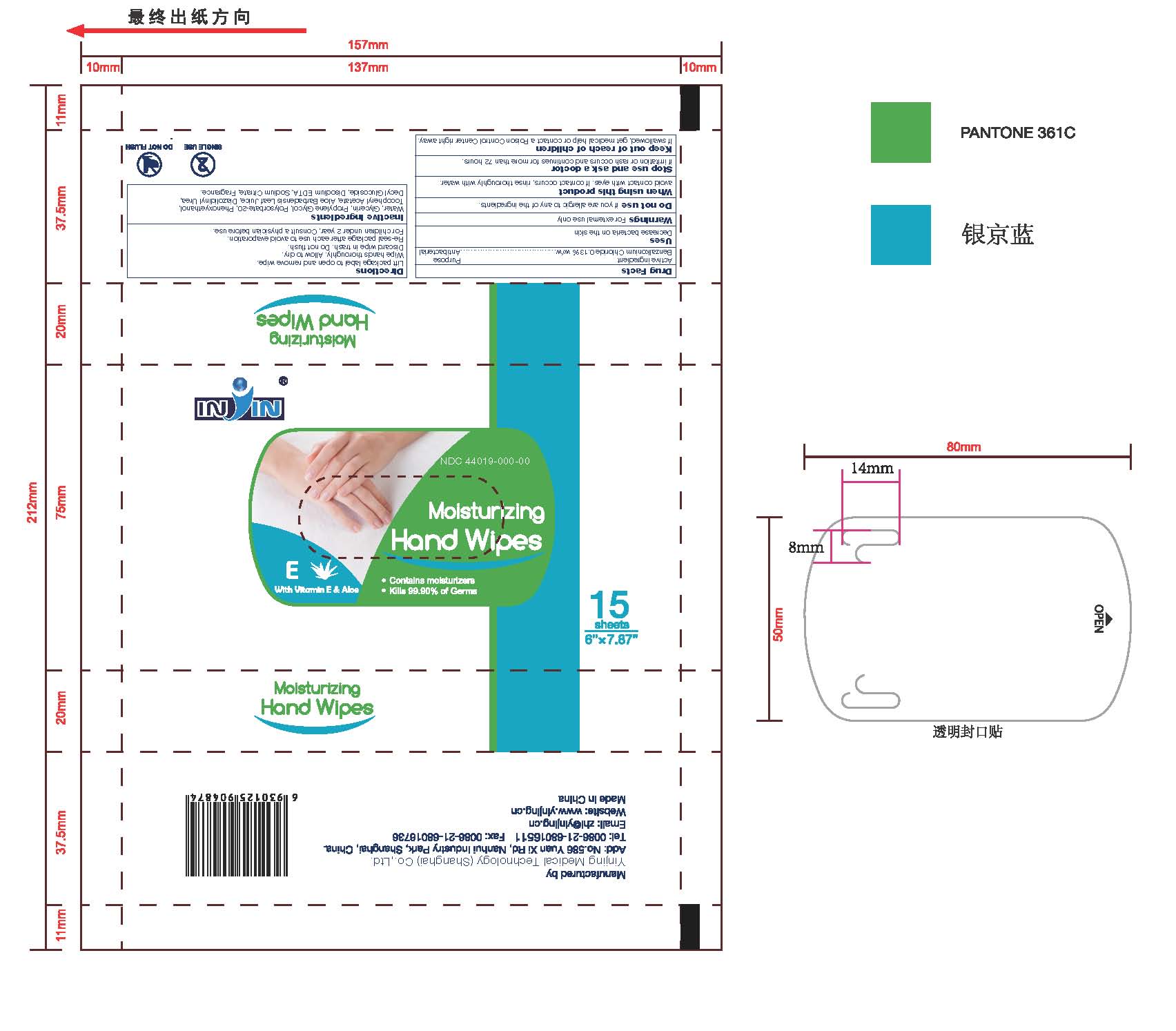 DRUG LABEL: Antibacterial Moisturizing Hand Wipes
NDC: 44019-000 | Form: LIQUID
Manufacturer: Yinjing Medical Technology (Shanghai) Co., Ltd.
Category: otc | Type: HUMAN OTC DRUG LABEL
Date: 20171227

ACTIVE INGREDIENTS: BENZALKONIUM CHLORIDE 0.13 g/100 g
INACTIVE INGREDIENTS: WATER; GLYCERIN; PROPYLENE GLYCOL; POLYSORBATE 20; PHENOXYETHANOL; .ALPHA.-TOCOPHEROL ACETATE; ALOE VERA LEAF; DIAZOLIDINYL UREA; DECYL GLUCOSIDE; EDETATE DISODIUM; SODIUM CITRATE

Antibacterial Moisturizing Hand Wipes

Active ingredient

Benzalkonium Chloride 0.13%

Purpose

Antibacterial

Use

Decrease bacteria on the skin

Warnings

For external use only

Do not use

if you are allergic to any of the ingredients.

When using this product

avoid contact with eyes. If contact occurs, rinse thoroughly with water.

Stop use and ask a doctor

if irritation or rash occurs and continues for more than 72 hours.

Keep out of reach of children

If swallowed, get medical help or contact a Poison Control Center right away.

Directions

Lift package label to open and remove wipe.
Wipe hands thoroughly. Allow to dry.
Discard wipe in trash. Do not flush.
Re-seal package after each use to avoid evaporation.
For children under 2 year, Consult a physician before use.

Inactive ingredients

Water, Glycerin, Propylene Glycol, Polysorbate-20, Phenoxyethanol, Tocopheryl Acetate, Aloe Barbadensis Leaf Juice, Diazolidinyl Urea, Decyl Glucoside, Disodium EDTA, Sodium Citrate, Fragrance.

IN IN

Shanghai Yinjing Medical Supplies Co.,Ltd.
Add: No.586YuanXi Rd, Nanhui Industry Park,
Pudong new area,Shanghai.China.
Tel:+86-(21)68016511 Fax:+86-(21)68016736
http://www.yinjing.cn E-mail:zhl@yinjing.cn

PACKAGE LABEL

IN IN NDC: Antibacterial Moisturizing Hand Wipes 15 wipes 5.12 x 7.87 in (13cm x 20 cm) Kills 99.9% of Germs Contains Moisturizers, Vitamin E and Aloe